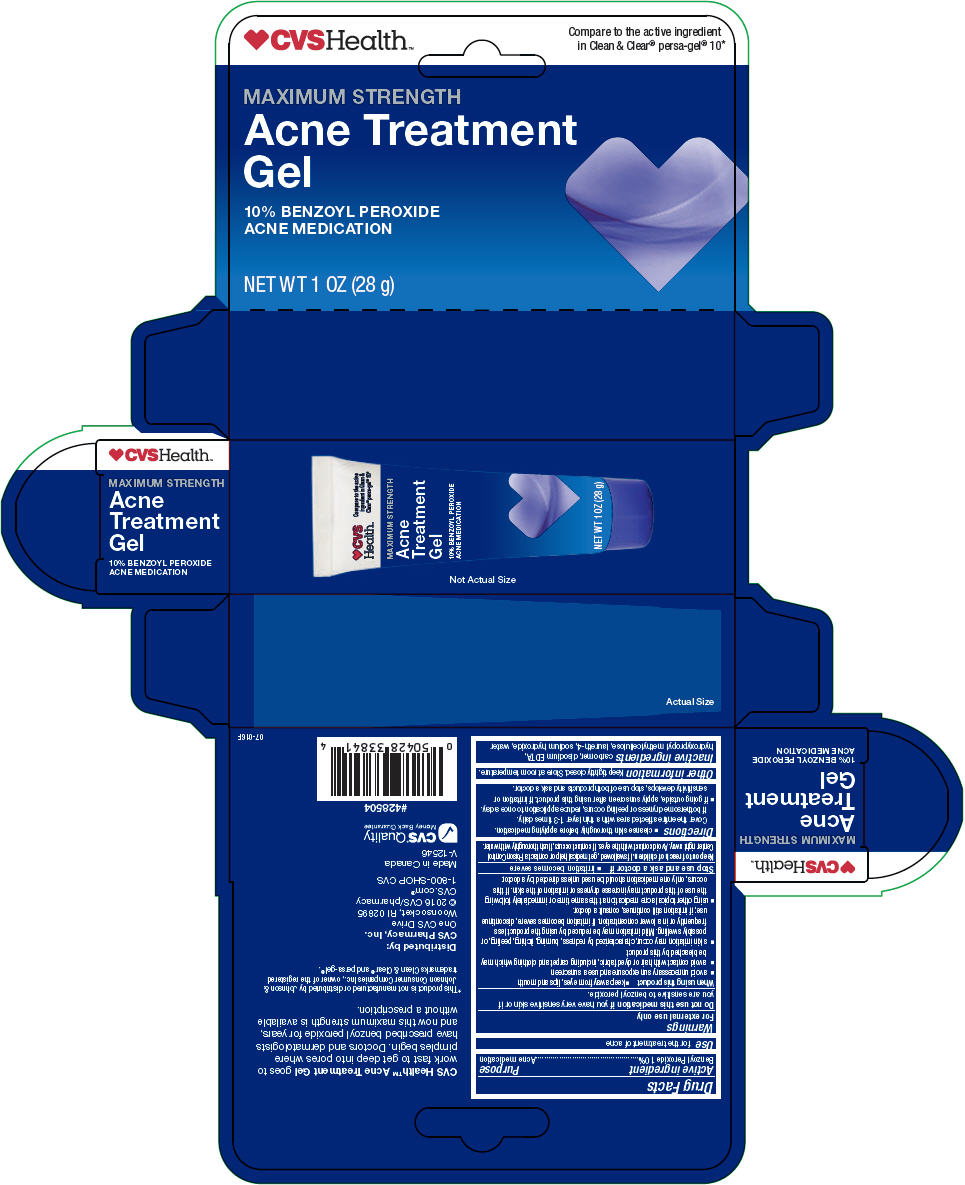 DRUG LABEL: CVS Health Maximum Strength Acne Treatment 
NDC: 69842-637 | Form: GEL
Manufacturer: CVS Health
Category: otc | Type: HUMAN OTC DRUG LABEL
Date: 20220124

ACTIVE INGREDIENTS: Benzoyl Peroxide 100 mg/1 mL
INACTIVE INGREDIENTS: CARBOXYMETHYLCELLULOSE SODIUM, UNSPECIFIED; Edetate Disodium; Hypromellose, Unspecified; Laureth-4; Sodium Hydroxide; Water

CVS Health™ Maximum Strength Acne Treatment Gel
Acne Medication

Drug Facts

Active ingredient

Benzoyl Peroxide 10%

Purpose

Acne medication

Use

for the treatment of acne

Warnings

For external use only

Do not use this medication if you have very sensitive skin or if you are sensitive to benzoyl peroxide.

When using this product

- keep away from eyes, lips and mouth
- avoid unnecessary sun exposure and use a sunscreen
- avoid contact with hair or dyed fabric, including carpet and clothing which may be bleached by this product
- skin irritation may occur, characterized by redness, burning, itching, peeling, or possibly swelling. Mild irritation may be reduced by using the product less frequently or in a lower concentration. If irritation becomes severe, discontinue use; if irritation still continues, consult a doctor.
- using other topical acne medication at the same time or immediately following the use of this product may increase dryness or irritation of the skin. If this occurs, only one medication should be used unless directed by a doctor.

Stop use and ask a doctor if

- irritation becomes severe

Keep out of reach of children. If swallowed, get medical help or contact a Poison Control Center right away. Avoid contact with the eyes. If contact occurs, flush thoroughly with water.

Directions

- cleanse skin thoroughly before applying medication. Cover the entire affected area with a thin layer 1-3 times daily. If bothersome dryness or peeling occurs, reduce application to once a day.
- if going outside, apply sunscreen after using this product. If irritation or sensitivity develops, stop use of both products and ask a doctor.

Other information

Keep tightly closed. Store at room temperature.

Inactive ingredients

carbomer, disodium EDTA, hydroxypropyl methylcellulose, laureth-4, sodium hydroxide, water

Distributed by:
CVS Pharmacy, Inc.
One CVS Drive
Woonsocket, RI 02895

PRINCIPAL DISPLAY PANEL - 28 g Tube Carton

CVSHealth™

Compare to the active ingredient
in Clean & Clear® persa-gel® 10*

MAXIMUM STRENGTH

Acne Treatment
Gel

10% BENZOYL PEROXIDE
ACNE MEDICATION

NET WT 1 OZ (28 g)

Not Actual Size